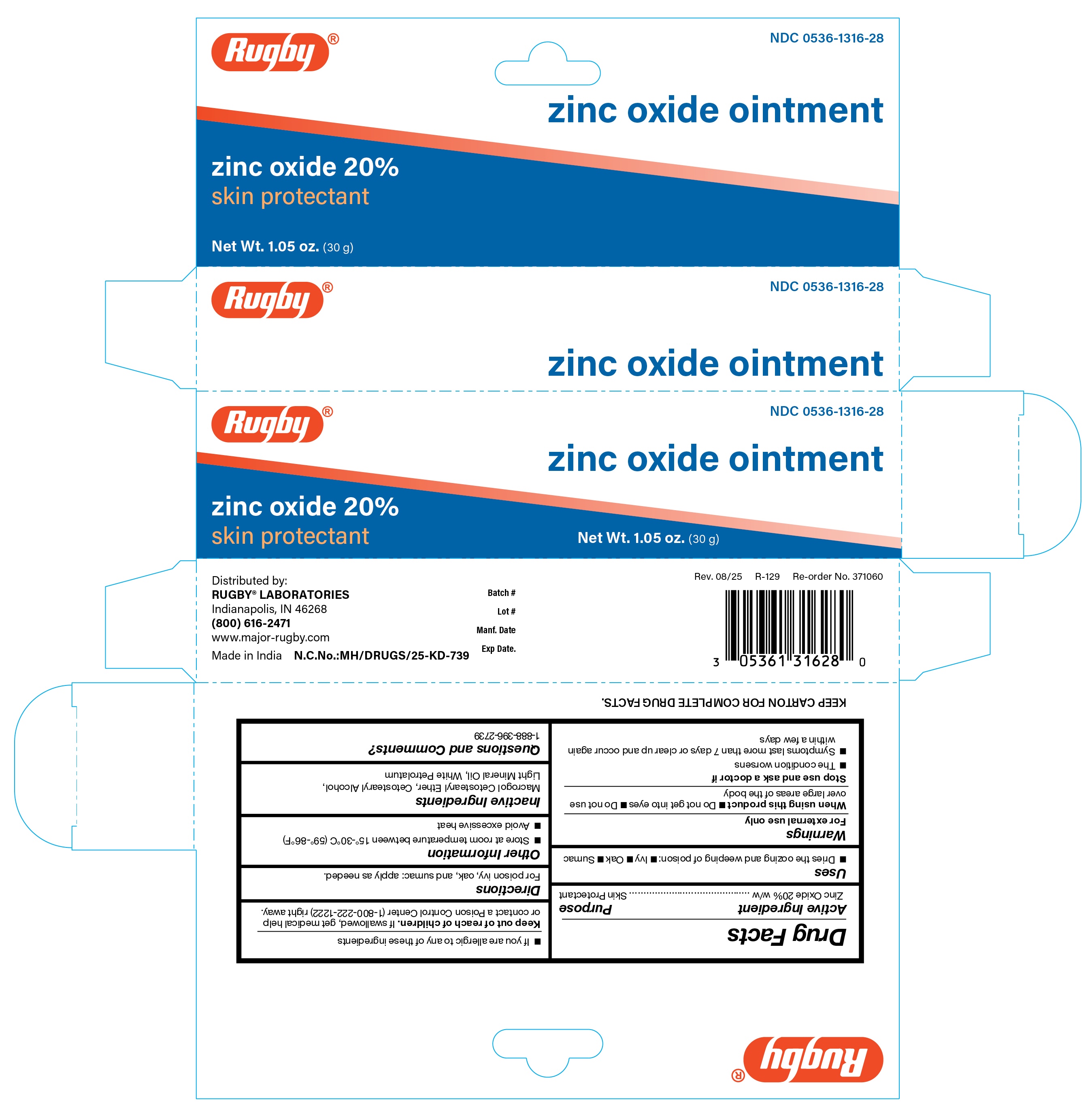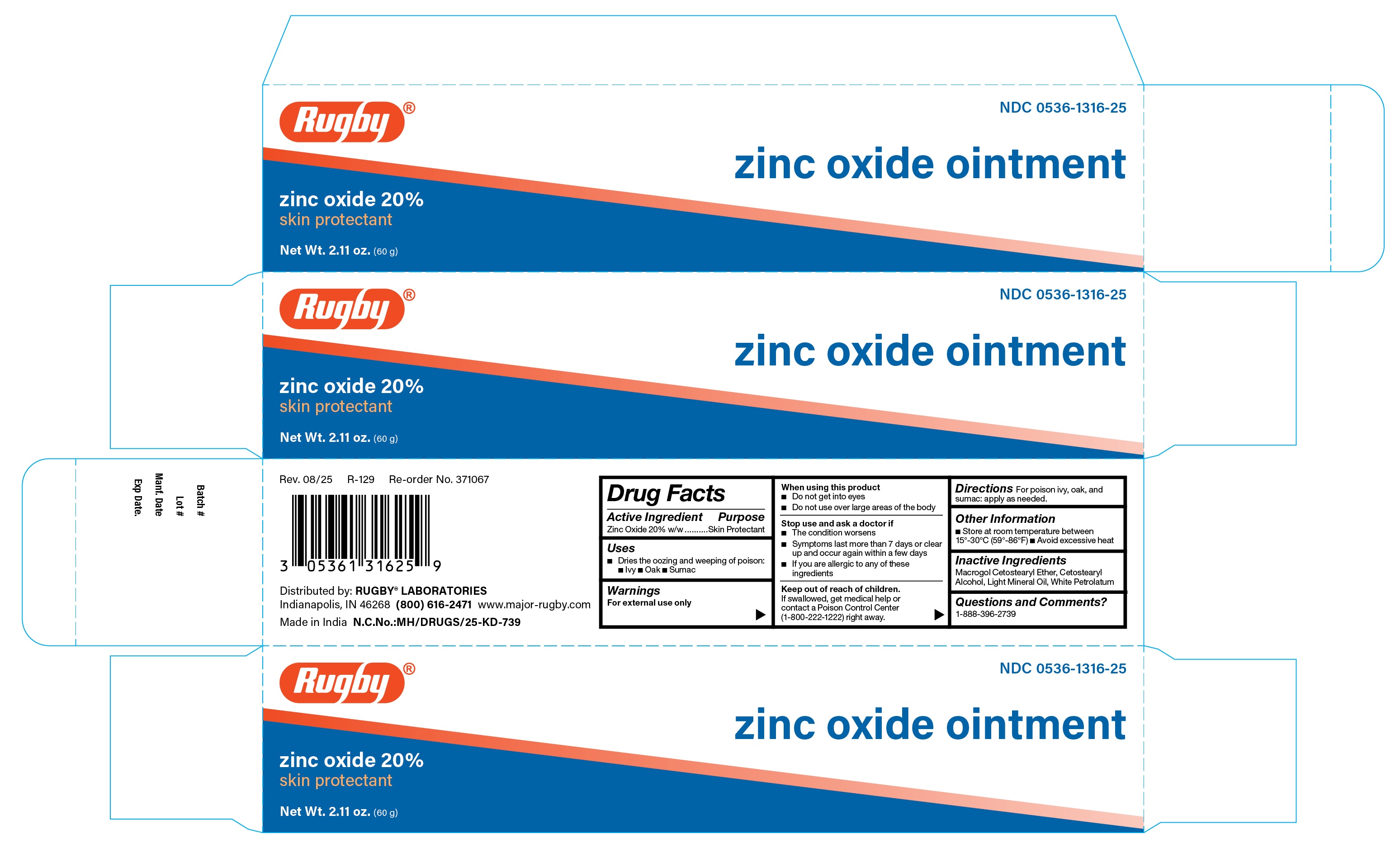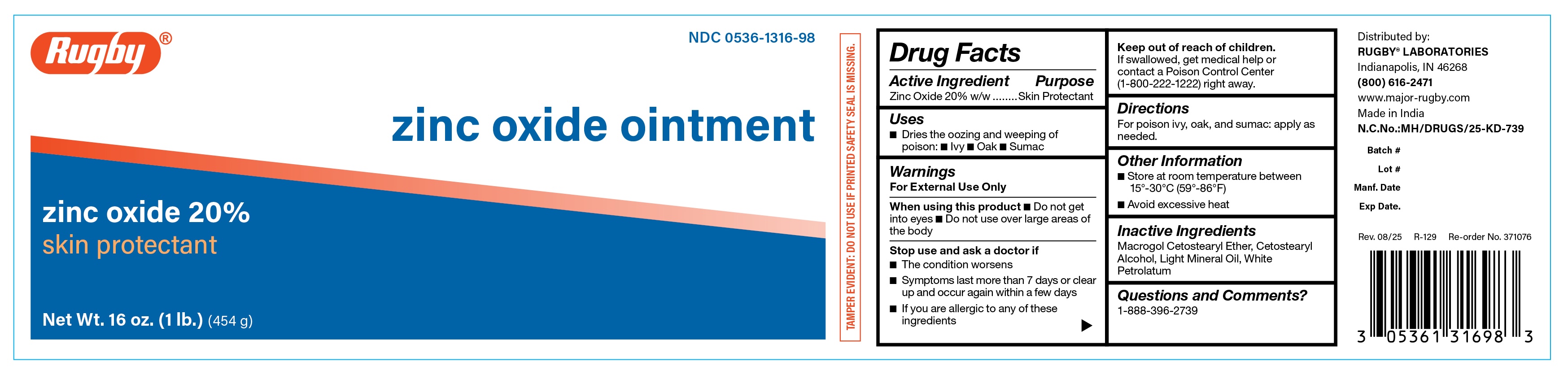 DRUG LABEL: Rugby Zinc Oxide 20%
NDC: 0536-1316 | Form: OINTMENT
Manufacturer: Rugby Laboratories
Category: otc | Type: HUMAN OTC DRUG LABEL
Date: 20251125

ACTIVE INGREDIENTS: ZINC OXIDE 20 g/100 g
INACTIVE INGREDIENTS: LIGHT MINERAL OIL; CETOSTEARYL ALCOHOL; CETETH-20; PETROLATUM

CR-371076 Rugby Zinc Oxide 20%
CR-371060 Rugby Zinc Oxide 20%
CR-371067 Rugby Zinc Oxide 20%

Active Ingredient

Zinc Oxide 20% w/w

Purpose

Skin Protectant

Uses

• Dries the oozing and weeping of poison: • Ivy • Oak • Sumac

Warnings

For External Use Only

When using this product

• Do not get into eyes

• Do not use over large areas of the body

Stop use and ask a doctor if

• The condition worsens

• Symptoms last more than 7 days or clear up and occur again within a few days

• If you are allergic to any of these ingredients

Keep out of reach of children

If swallowed, get medical help or contact a Poison Control Center (1-800-222-1222) right away.

Directions

For poison ivy, oak, and sumac: apply as needed.

Other Information

• Store at room temperature between 15°-30°C (59°-86°F)

• Avoid excessive heat

Inactive Ingredients

Cetomacrogol 1000, Cetostearyl Alcohol, Light Mineral Oil, White Soft Paraffin (Petrolatum)

Questions and Comments?

1-800-645-2158

Label

CR-371060 Label

Label

CR-371076 Label

Label

CR-371067 Label